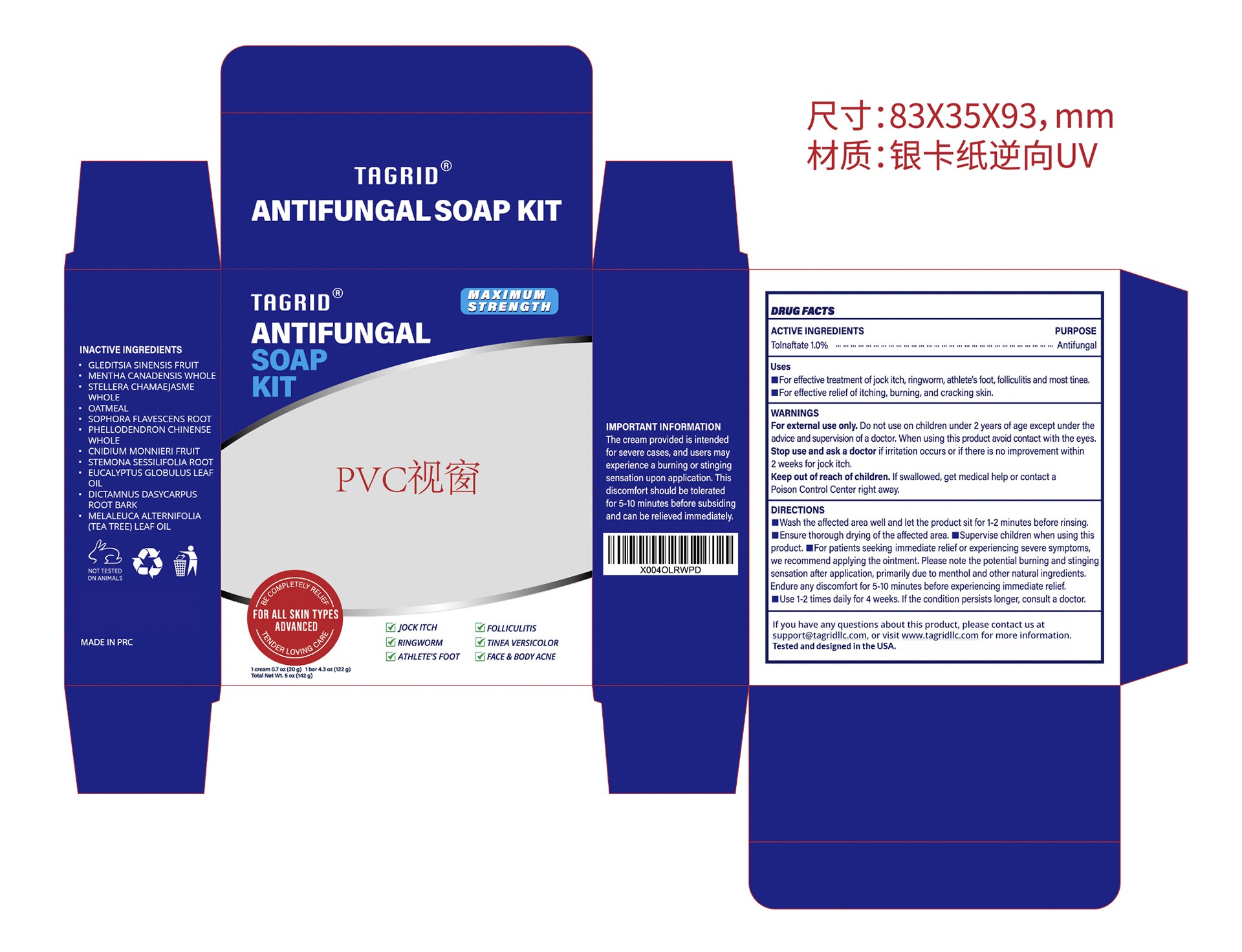 DRUG LABEL: Tagrid Antifungal
NDC: 85384-0010 | Form: SOAP
Manufacturer: TAGRID LLC
Category: otc | Type: HUMAN OTC DRUG LABEL
Date: 20250609

ACTIVE INGREDIENTS: TOLNAFTATE 10 mg/1 g
INACTIVE INGREDIENTS: GLEDITSIA SINENSIS FRUIT; MENTHA CANADENSIS WHOLE; STELLERA CHAMAEJASME WHOLE; OATMEAL; SOPHORA FLAVESCENS ROOT; PHELLODENDRON CHINENSE WHOLE; CNIDIUM MONNIERI FRUIT; STEMONA SESSILIFOLIA ROOT; EUCALYPTUS GLOBULUS LEAF OIL; DICTAMNUS DASYCARPUS ROOT BARK; MELALEUCA ALTERNIFOLIA (TEA TREE) LEAF OIL

Initial Drug Listing-Tagrid Antifungal Soap Kit

ACTIVE INGREDIENT

Tolnaftate

Uses
For effective treatment of jock itch, ringworm, athlete's foot, folliculitnost tinea
For effective relief of itching, burning, and cracking sking skin.

WARNINGS

For external use only

Do not use on children under 2 years of age exceptunder the advice and supervision of a doctor.

When using this product avoid contact with the eyes.

Stop use and ask a doctor if irritation occurs or if there is no improvement within 2weeks for jock itch.

Keep out of reach of children. If swallowed, get medical help or contact a Poison Control Center right away.

DIRECTIONS
Wash the affected area well and let the product sit for 1-2 minutes before rising
Ensure thorough drying of the affected area.

Supervise children when using this product.

For patients seeking immediate relief or experiencing severe symptoms, we recommend applying the ointment. Please note the potential burning and stinging sensation after application, primarily due to menthol and other natural ingredients.
Endure any discomfort for 5-10 minutes before experiencing immediate relief.
Use 1-2 times daily for 4 weeks. If the condition persists longer, consult a doctor.

OTHER SAFETY INFORMATION

The cream provided is intended for severe cases, and users may experience a burning or stinging sensation upon application. This discomfort should be tolerated for 5-10 minutes before subsiding and can be relieved immediately.

QUESTIONS

If you have any questions about this product, please contact us at support@tagridllc.com, or visit www.tagridllc.com for more information.
Tested and designed in the USA.

INACTIVE INGREDIENT

GLEDITSIA SINENSIS FRUIT
MENTHA CANADENSIS WHOLE
STELLERA CHAMAEJASME WHOLE
OATMEAL
SOPHORA FLAVESCENS ROOT
PHELLODENDRON CHINENSE WHOLE
CNIDIUM MONNIERI FRUIT
STEMONA SESSILIFOLIA ROOT
EUCALYPTUS GLOBULUS LEAF OIL
DICTAMNUS DASYCARPUS ROOT BARK
MELALEUCA ALTERNIFOLIA (TEA TREE) LEAF OIL